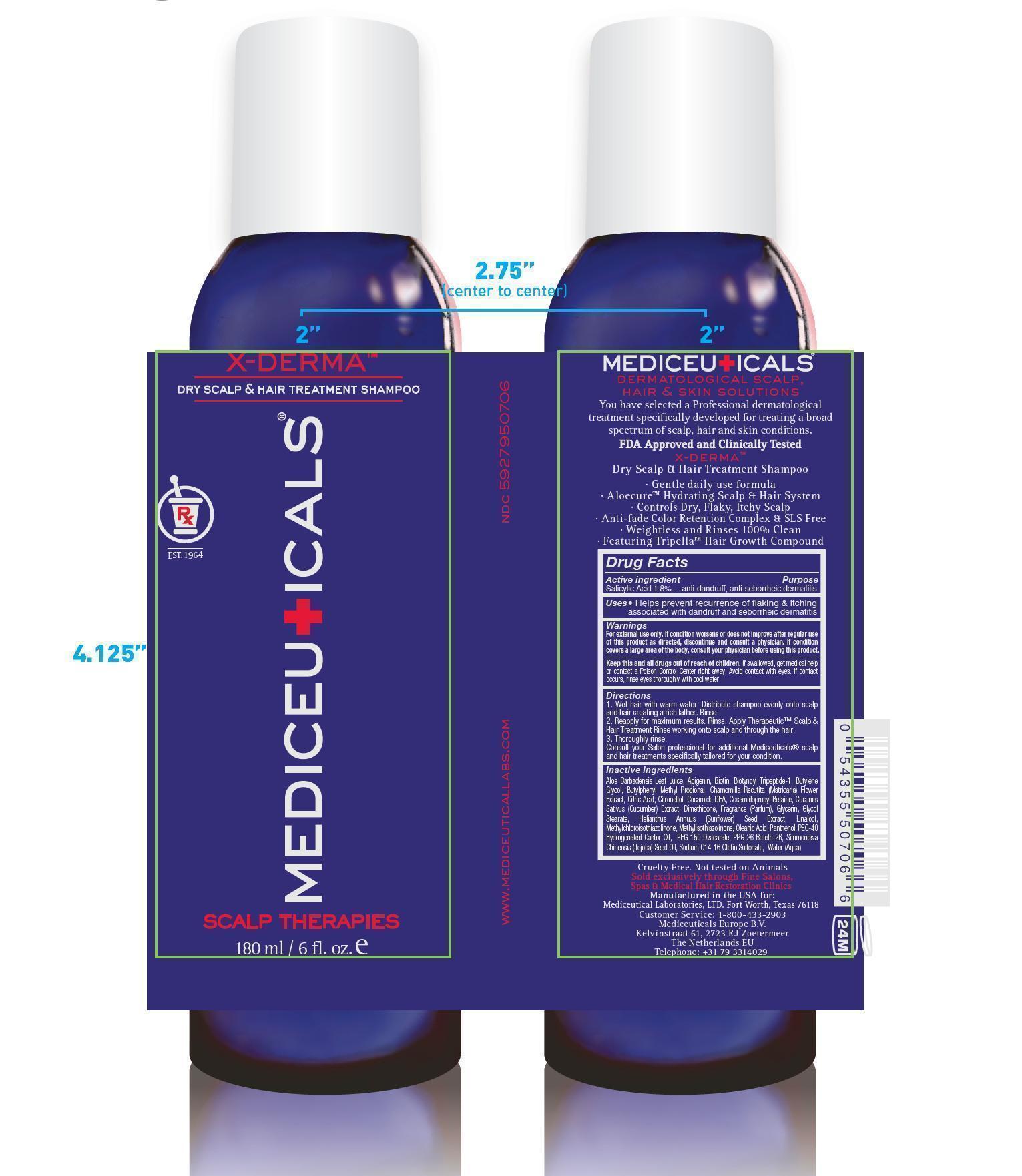 DRUG LABEL: Mediceuticals X-Derma
NDC: 59279-507 | Form: SHAMPOO
Manufacturer: Mediceutical Laboratories, Ltd.
Category: otc | Type: HUMAN OTC DRUG LABEL
Date: 20151228

ACTIVE INGREDIENTS: SALICYLIC ACID 1.8 g/100 mL
INACTIVE INGREDIENTS: ALOE VERA LEAF; APIGENIN; BIOTIN; BIOTINOYL TRIPEPTIDE-1; 1-BUTENE; BUTYLPHENYL METHYLPROPIONAL; CHAMOMILE; CITRIC ACID MONOHYDRATE; .BETA.-CITRONELLOL, (R)-; COCO DIETHANOLAMIDE; COCAMIDOPROPYL BETAINE; CUCUMBER SEED; DIMETHICONE; GLYCERIN; SUNFLOWER SEED; METHYLCHLOROISOTHIAZOLINONE; METHYLISOTHIAZOLINONE; PANTHENOL; POLYOXYL 40 HYDROGENATED CASTOR OIL; PEG-150 DISTEARATE; SIMMONDSIA CHINENSIS SEED WAX; SODIUM C14-16 OLEFIN SULFONATE; WATER

Mediceutical Laboratories X-Derma Dry Scalp and Hair Treatment - Drug Facts

Active Ingredient

Salicylic Acid 1.8%

Purpose

Anti-dandruff, anti-seborrheic dermatitis

Uses

Helps prevent recurrence of flaking and itching
associated with dandruff and seborrheic dermatitis.

Warnings

For external use only. If condition worsens or does not improve after regular use of this product as directed, discontinue and consult a physician. If condition covers a large area of the body, consult your physician before using this product.

Keep this and all drugs out of reach of children.

If swallowed, get medical help or contact a Poison Control Center right away. Avoid contact with eyes. If contact occurs, rinse eyes thoroughly with cool water.

Directions

1. Wet hair with warm water. Distribute shampoo evenly onto scalp
and hair creating a rich lather. Rinse.
2. Reapply for maximum results. Rinse. Apply Therapeutic™ Scalp and
Hair Treatment Rinse working onto scalp and through the hair.
3. Thoroughly rinse.
Consult your Salon professional for additional Mediceuticals® scalp
and hair treatments specifically tailored for your condition.

Inactive Ingredients

Aloe Barbadensis Leaf Juice, Apigenin, Biotin, Biotynoyl Tripeptide-1, Butylene
Glycol, Butylphenyl Methyl Propional, Chamomilla Recutita (Matricaria) Flower
Extract, Citric Acid, Citronellol, Cocamide DEA, Cocamidopropyl Betaine, Cucumis
Sativus (Cucumber) Extract, Dimethicone, Fragrance (Parfum), Glycerin, Glycol
Stearate, Helianthus Annuus (Sunflower) Seed Extract, Linalool, Methylchloroisothiazolinone,
Methylisothiazolinone, Oleanic Acid, Panthenol, PEG-40 Hydrogenated
Castor Oil, PEG-150 Distearate, PPG-26-Buteth-26, Simmondsia Chinensis
(Jojoba) Seed Oil, Sodium C14-16 Olefin Sulfonate, Water (Aqua)

Image of Label

MediceuticalXDermaLabel180mL.jpg